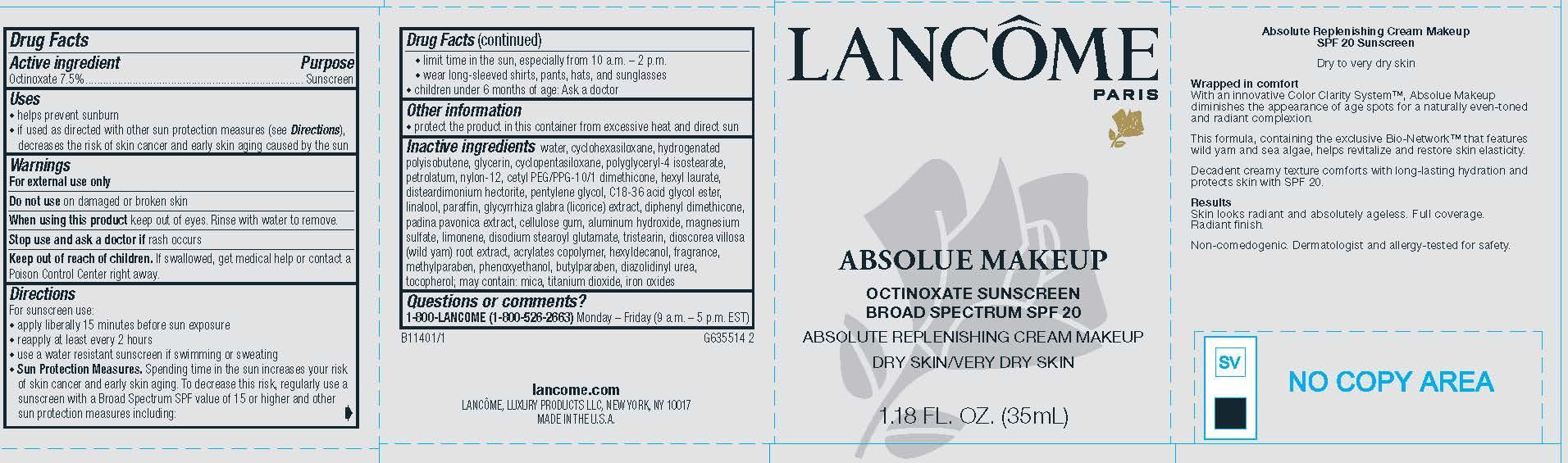 DRUG LABEL: Lancome Paris Absolue Makeup Broad Spectrum SPF 20 Sunscreen Absolute Replenishing Makeup for Dry and Very Dry Skin
NDC: 49967-596 | Form: CREAM
Manufacturer: L'Oreal USA Products Inc
Category: otc | Type: HUMAN OTC DRUG LABEL
Date: 20240628

ACTIVE INGREDIENTS: OCTINOXATE 75 mg/1 mL
INACTIVE INGREDIENTS: WATER; CYCLOMETHICONE 6; HYDROGENATED POLYISOBUTENE (450 MW); GLYCERIN; CYCLOMETHICONE 5; polyglyceryl-4 isostearate; petrolatum; nylon-12; CETYL PEG/PPG-10/1 DIMETHICONE (HLB 4); hexyl laurate; disteardimonium hectorite; pentylene glycol; LINALOOL, (+/-)-; Paraffin; DIPHENYL DIMETHICONE (300 CST); PADINA PAVONICA; CARBOXYMETHYLCELLULOSE SODIUM, UNSPECIFIED; aluminum hydroxide; MAGNESIUM SULFATE, UNSPECIFIED FORM; LIMONENE, (+)-; disodium stearoyl glutamate; tristearin; DIOSCOREA VILLOSA TUBER; LUVISET 360; hexyldecanol; methylparaben; phenoxyethanol; butylparaben; diazolidinyl urea; tocopherol; mica; titanium dioxide; FERRIC OXIDE RED

Drug Facts

Active ingredient

Octinoxate 7.5%

Purpose

Sunscreen

Uses

- helps prevent sunburn
- if used as directed with other sun protection measures (see Directions), decreases the risk of skin cancer and early skin aging caused by the sun

Warnings

For external use only

Do not use

on damaged or broken skin

When using this product

keep out of eyes. Rinse with water to remove.

Stop use and ask a doctor if

rash occurs

Keep out of reach of children.

If swallowed, get medical help or contact a Poison Control Center right away.

Directions

For sunscreen use:

● apply liberally 15 minutes before sun exposure

● reapply at least every 2 hours

● use a water resistant sunscreen if swimming or sweating

● Sun Protection Measures. Spending time in the sun increases your risk of skin cancer and early skin aging. To decrease this risk, regularly use a sunscreen with a Broad Spectrum SPF value of 15 or higher and other sun protection measures including:

● limit time in the sun, especially from 10 a.m. – 2 p.m.

● wear long-sleeved shirts, pants, hats, and sunglasses

● children under 6 months of age: Ask a doctor

Other information

protect the product in this container from excessive heat and direct sun

Inactive ingredients

water, cyclohexasiloxane, hydrogenated polyisobutene, glycerin, cyclopentasiloxane, polyglyceryl-4 isostearate, petrolatum, nylon-12, cetyl PEG/PPG-10/1 dimethicone, hexyl laurate, disteardimonium hectorite, pentylene glycol, C18-36 acid glycol ester, linalool, paraffin, glycyrrhiza glabra (licorice) extract, diphenyl dimethicone, padina pavonica extract, cellulose gum, aluminum hydroxide, magnesium sulfate, limonene, disodium stearoyl glutamate, tristearin, dioscorea villosa (wild yam) root extract, acrylates copolymer, hexyldecanol, fragrance, methylparaben, phenoxyethanol, butylparaben, diazolidinyl urea, tocopherol; may contain: mica, titanium dioxide, iron oxides

Questions or comments?

1-800-LANCOME (1800-526-2663) Monday - Friday (9 a.m. - 5 p.m. EST)